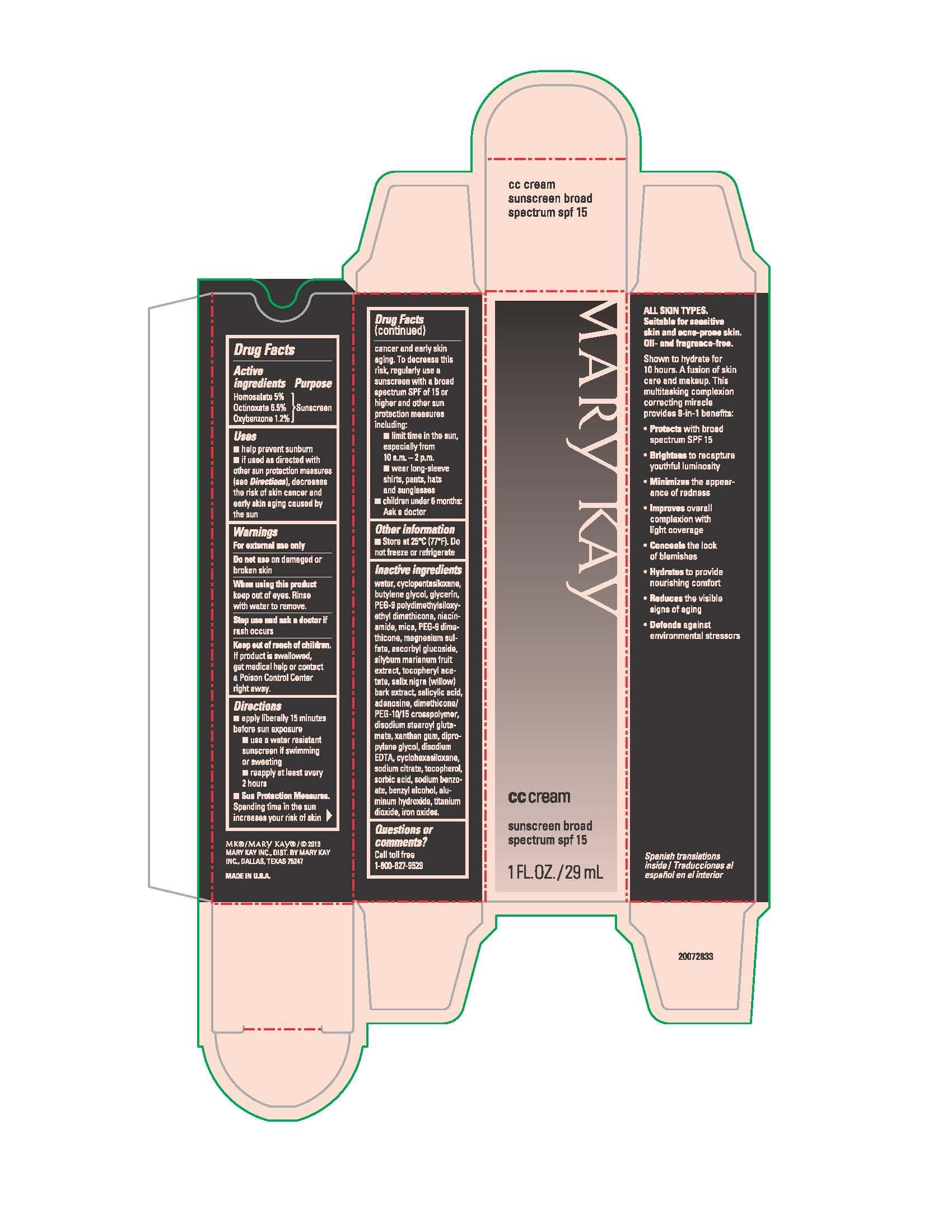 DRUG LABEL: Mary Kay CC Cream Sunscreen Broad Spectrum SPF 15 Deep
NDC: 51531-2825 | Form: CREAM
Manufacturer: Mary Kay Inc.
Category: otc | Type: HUMAN OTC DRUG LABEL
Date: 20241217

ACTIVE INGREDIENTS: HOMOSALATE 5 g/100 mL; OCTINOXATE 6.5 g/100 mL; OXYBENZONE 1.2 g/100 mL
INACTIVE INGREDIENTS: DIMETHICONE/PEG-10/15 CROSSPOLYMER; WATER; CYCLOMETHICONE 5; BUTYLENE GLYCOL; GLYCERIN; PEG-9 POLYDIMETHYLSILOXYETHYL DIMETHICONE; NIACINAMIDE; MICA; PEG-9 DIMETHICONE (400 CST); MAGNESIUM SULFATE, UNSPECIFIED FORM; ASCORBYL GLUCOSIDE; MILK THISTLE; .ALPHA.-TOCOPHEROL ACETATE; SALIX NIGRA BARK; SALICYLIC ACID; ADENOSINE; DISODIUM STEAROYL GLUTAMATE; XANTHAN GUM; DIPROPYLENE GLYCOL; EDETATE DISODIUM; CYCLOMETHICONE 6; SODIUM CITRATE, UNSPECIFIED FORM; TOCOPHEROL; SORBIC ACID; SODIUM BENZOATE; BENZYL ALCOHOL; ALUMINUM HYDROXIDE; FERRIC OXIDE RED; FERRIC OXIDE YELLOW; FERROSOFERRIC OXIDE; TITANIUM DIOXIDE

Mary Kay CC Cream Sunscreen SPF 15 Deep
Drug Facts

Active ingredients

Homosalate 5%

Octinoxate 6.5%

Oxybenzone 1.2 %

Purpose

Sunscreen

Uses

- helps prevent sunburn
- if used as directed with other sun protection measures (see Directions), decreases the risk of skin cancer and early skin aging caused by the sun

Warnings

For external use only

Do not use

on damaged or broken skin

When using this product

keep out of eyes. Rinse with water to remove.

Stop use and ask a doctor

if rash occurs

Keep out of reach of children.

If product is swallowed, get medical help or contact a Poison Control Center right away.

Directions

- apply liberally 15 minutes before sun exposure
- use a water resistant sunscreen if swimming or sweating
- reapply at least every 2 hours
- Sun Protection Measures. Spending time in the sun increases your risk of skin cancer and early skin aging. To decrease this risk, regularly use a sunscreen with a broad spectrum SPF of 15 or higher and other sun protection measures including:
- limit time in the sun, especially from 10 a.m. - 2 p.m.
- wear long-sleeve shirts, pants, hats and sunglasses
- children under 6 months: Ask a doctor

Other information

- Store at 25°C (77°F). Do not freeze or refrigerate.

Inactive ingredients

water, cyclopentasiloxane, butylene glycol, glycerin, PEG-9 polydimethylsiloxyethyl dimethicone, niacinamide, mica, PEG-9 dimethicone, magnesium sulfate, ascorbyl glucoside, silybum marianum fruit extract, tocopheryl acetate, salix nigra (willow) bark extract, salicylic acid, adenosine, dimethicone/PEG-10/15 crosspolymer, disodium stearoyl glutamate, xanthan gum, dipropylene glycol, disodium EDTA, cyclohexasiloxane, sodium citrate, tocopherol, sorbic acid, sodium benzoate, benzyl alcohol, aluminum hydroxide, titanium dioxide, iron oxides

Questions or comments?

Call toll free 1-800-627-9529

Principal Display Panel - 29 mL carton

Mary Kay

cc cream

sunscreen broad

spectrum spf 15

cream

1 FL. OZ. / 29 mL